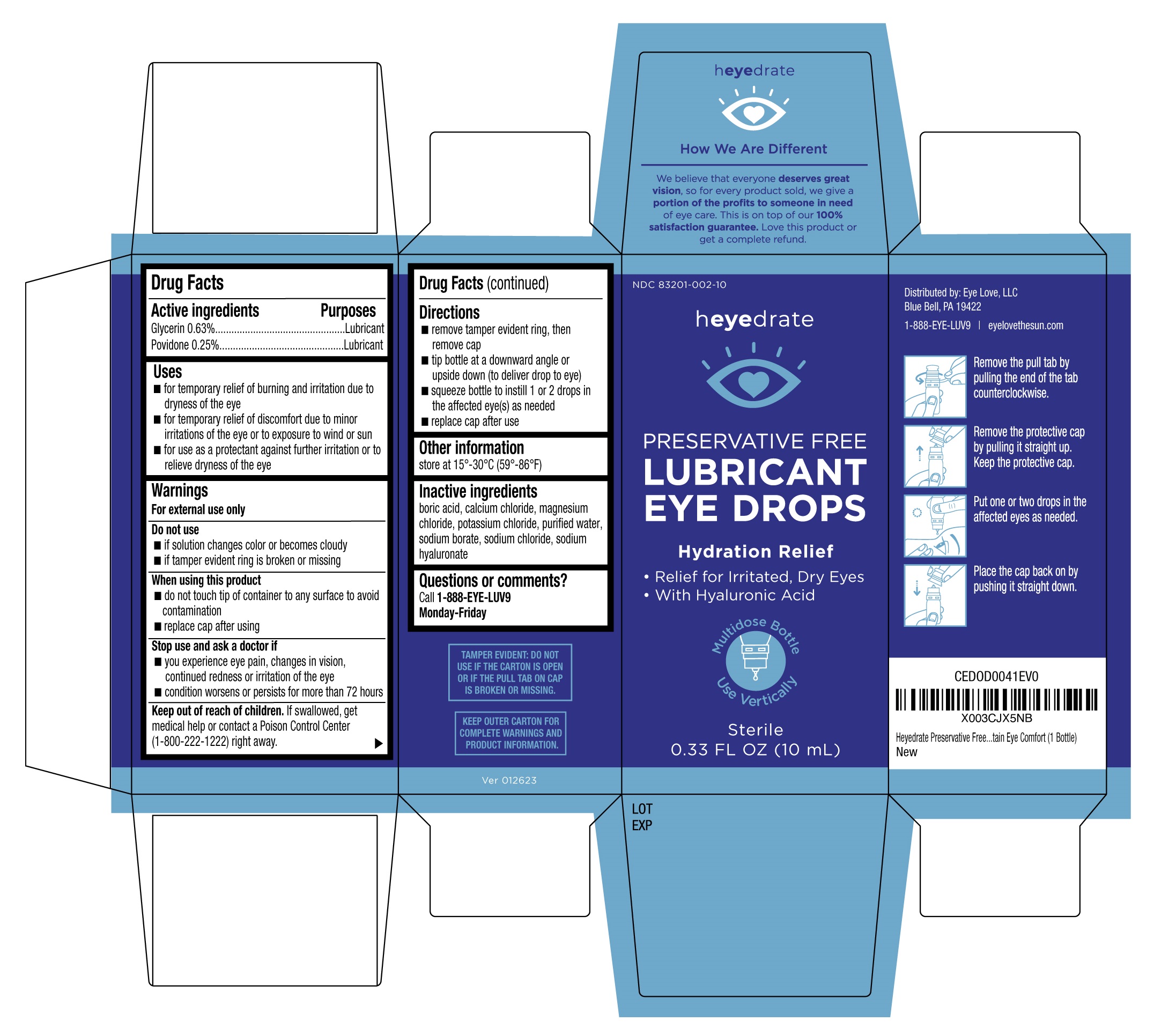 DRUG LABEL: Eye Love Heyedrate Long Lasting Hydration
NDC: 83201-002 | Form: SOLUTION/ DROPS
Manufacturer: Physician Recommended Neutraceuticals, L.P.
Category: otc | Type: HUMAN OTC DRUG LABEL
Date: 20251230

ACTIVE INGREDIENTS: POVIDONE 0.25 g/100 mL; GLYCERIN 0.63 g/100 mL
INACTIVE INGREDIENTS: HYALURONATE SODIUM; BORIC ACID; CALCIUM CHLORIDE; WATER; SODIUM CHLORIDE; SODIUM BORATE; POTASSIUM CHLORIDE; MAGNESIUM CHLORIDE

Eye Love Heyedrate Lubricant Eye Drops 10mL (PLD)

Active ingredients

Glycerin 0.63%

Povidone 0.25%

Purpose

Lubricant

Lubricant

Uses

- for the temporary relief of burning and irritation due to dryness of the eye
- for the temporary relief of discomfort due to minor irritations of the eye or to exposure to wind or sun
- for use as a protectant against further irritation or to relieve dryness of the eye

Warnings

For external use only

Do not use

- if solution changes color or becomes cloudy
- if tamper evident ring is broken or missing

When using this product

- do not touch tip of container to any surface to avoid contamination
- replace cap after using

Stop use and ask a doctor if

- you experience eye pain, changes in vision, continued redness or irritation of the eye
- condition worsens or persists for more than 72 hours

Keep out of reach of childeren.

If swallowed, get medical help or contact a Poison Control Center (1-800-222-1222) right away.

Directions

- remove tamper evident ring, then remove cap
- tip bottle at a downward angle or upside down (to deliver drop to eye)
- squeeze bottle to instill 1 or 2 drops in the affected eye(s) as needed
- replace cap after use

Other information

store at 15°-30°C (59°-86°F)

Inactive ingredients

boric acid, calcium chloride, magnesium chloride, potassium chloride, purified water, sodium borate, sodium chloride, sodium hyaluronate

Questions or comments?

Call-1-888-EYE-LUV9

Monday-Friday